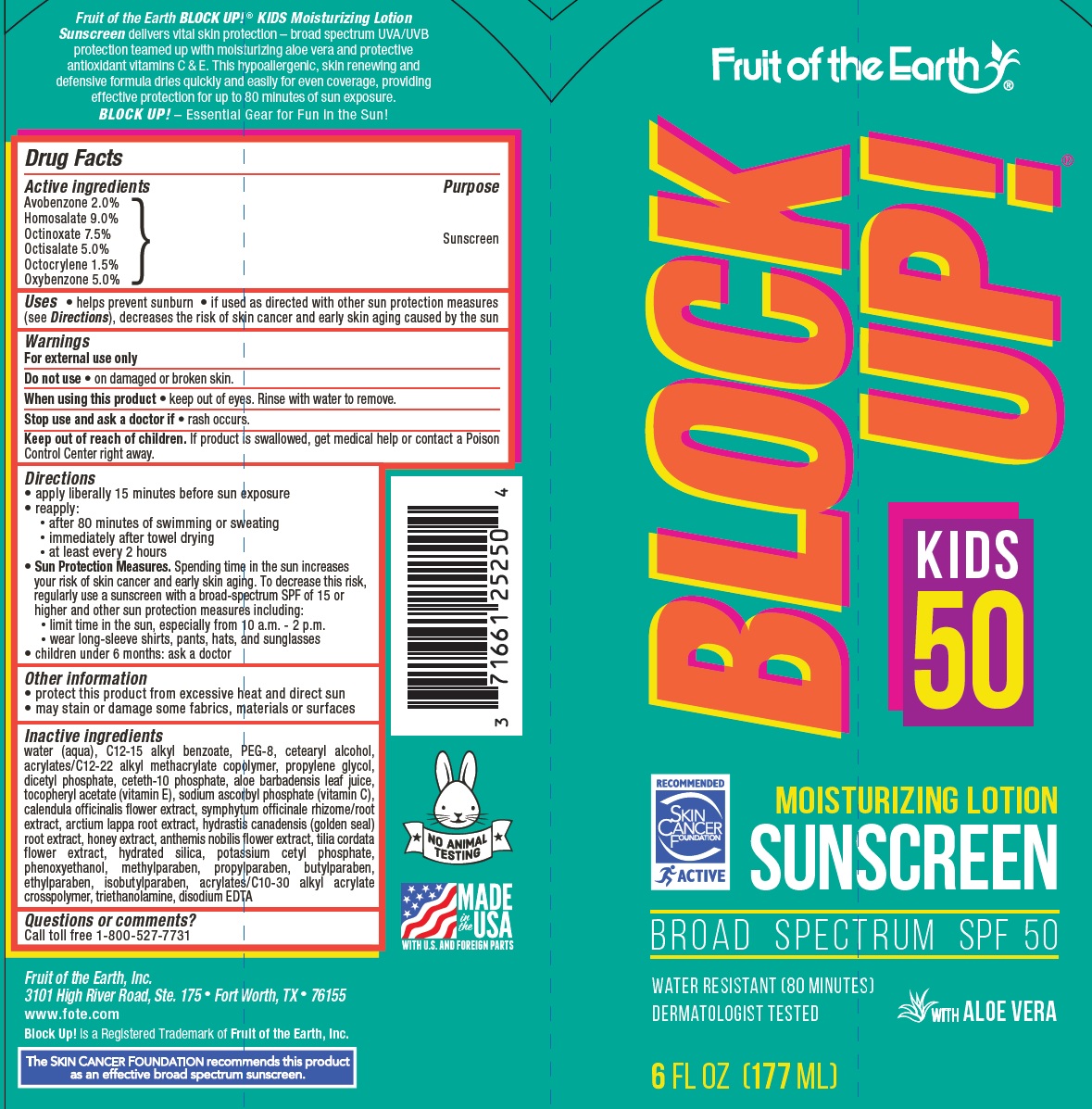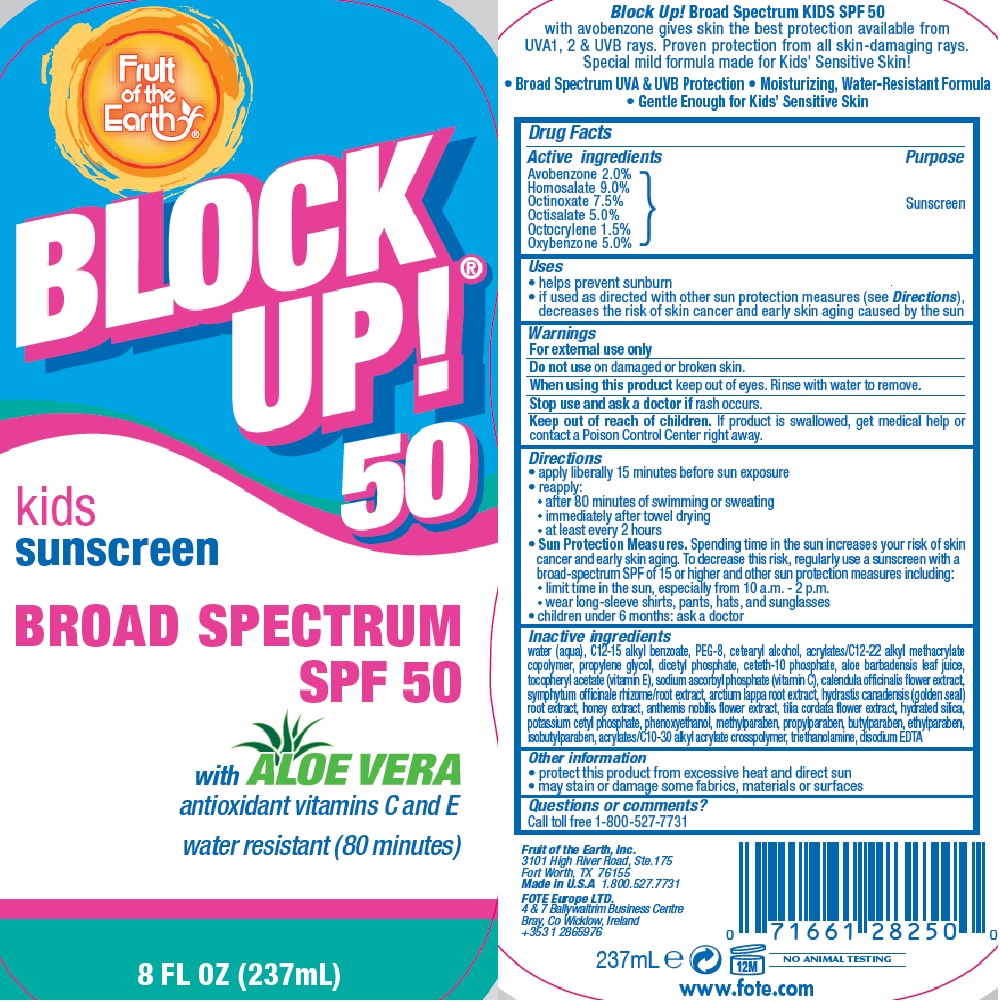 DRUG LABEL: Fruit of the Earth
NDC: 62217-013 | Form: LOTION
Manufacturer: Fruit of the Earth, Inc.
Category: otc | Type: HUMAN OTC DRUG LABEL
Date: 20170523

ACTIVE INGREDIENTS: AVOBENZONE 20 mg/1 mL; HOMOSALATE 90 mg/1 mL; OCTINOXATE 75 mg/1 mL; OCTISALATE 50 mg/1 mL; OXYBENZONE 50 mg/1 mL; OCTOCRYLENE 15 mg/1 mL
INACTIVE INGREDIENTS: BUTYL ACRYLATE/C16-C20 ALKYL METHACRYLATE/METHACRYLIC ACID/METHYL METHACRYLATE COPOLYMER; ALOE VERA LEAF; POTASSIUM CETYL PHOSPHATE; HYDRATED SILICA; CETETH-10 PHOSPHATE; DIHEXADECYL PHOSPHATE; ISOBUTYLPARABEN; CHAMAEMELUM NOBILE FLOWER; TROLAMINE; ETHYLPARABEN; PROPYLPARABEN; WATER; POLYETHYLENE GLYCOL 400; CETOSTEARYL ALCOHOL; CARBOMER INTERPOLYMER TYPE A (ALLYL SUCROSE CROSSLINKED); PROPYLENE GLYCOL; ALKYL (C12-15) BENZOATE; PHENOXYETHANOL; .ALPHA.-TOCOPHEROL ACETATE, D-; METHYLPARABEN; EDETATE DISODIUM ANHYDROUS; BUTYLPARABEN; SODIUM ASCORBYL PHOSPHATE; ARCTIUM LAPPA ROOT; CALENDULA OFFICINALIS FLOWER; HONEY; GOLDENSEAL; TILIA CORDATA WHOLE; COMFREY ROOT

Fruit of the Earth Block Up! Kids SPF 50 Moisturizing Sunscreen Lotion

Active ingredients

Avobenzone 2.0%, Homosalate 9.0%, Octinoxate 7.5%, Octisalate 5.0%, Octocrylene 1.5%, Oxybenzone 5.0%

Purpose

Sunscreen

Uses

• helps prevent sunburn • if used as directed with other sun protection measures (see Directions), decreases the risk of skin cancer and early skin aging caused by the sun

Warnings

For external use only

Do not use • on damaged or broken skin

When using this product

- keep out of eyes. Rinse with water to remove.

Stop use and ask a doctor if • rash occurs.

Keep out of reach of children. If swallowed, get medical help or contact a Poison Control Center right away.

Directions

• apply liberally 15 minutes before sun exposure • reapply: • after 80 minutes of swimming or sweating • immediately after towel drying • at least every 2 hours • Sun Protection Measures. Spending time in the sun increases your risk of skin cancer and early skin aging. To decrease this risk, regularly use a sunscreen with a broad-spectrum SPF of 15 or higher and other sun protection measures including: • limit time in the sun, especially from 10 a.m. - 2 p.m. • wear long-sleeve shirts, pants, hats, and sunglasses • children under 6 months: ask a doctor

Other information

• protect this product from excessive heat and direct sun • may stain or damage some fabrics, materials or surfaces

Inactive ingredients

water (aqua), C12-15 alkyl benzoate, PEG-8, cetearyl alcohol, acrylates/C12-22 alkyl methacrylate copolymer, propylene glycol, dicetyl phosphate, ceteth-10 phosphate, aloe barbadensis leaf juice, tocopheryl acetate (vitamin E), sodium ascorbyl phosphate (vitamin C), calendula officinalis flower extract, symphytum officinale rhizome/root extract, arctium lappa root extract, hydrastis canadensis (golden seal) root extract, honey extract, anthemis nobilis flower extract, tilia cordata flower extract, hydrated silica, potassium cetyl phosphate, phenoxyethanol, methylparaben, propylparaben, butylparaben, ethylparaben, isobutylparaben, acrylates/C10-30 alkyl acrylate crosspolymer, triethanolamine, disodium EDTA

Questions or Comments?

Call toll free 1-800-527-7731